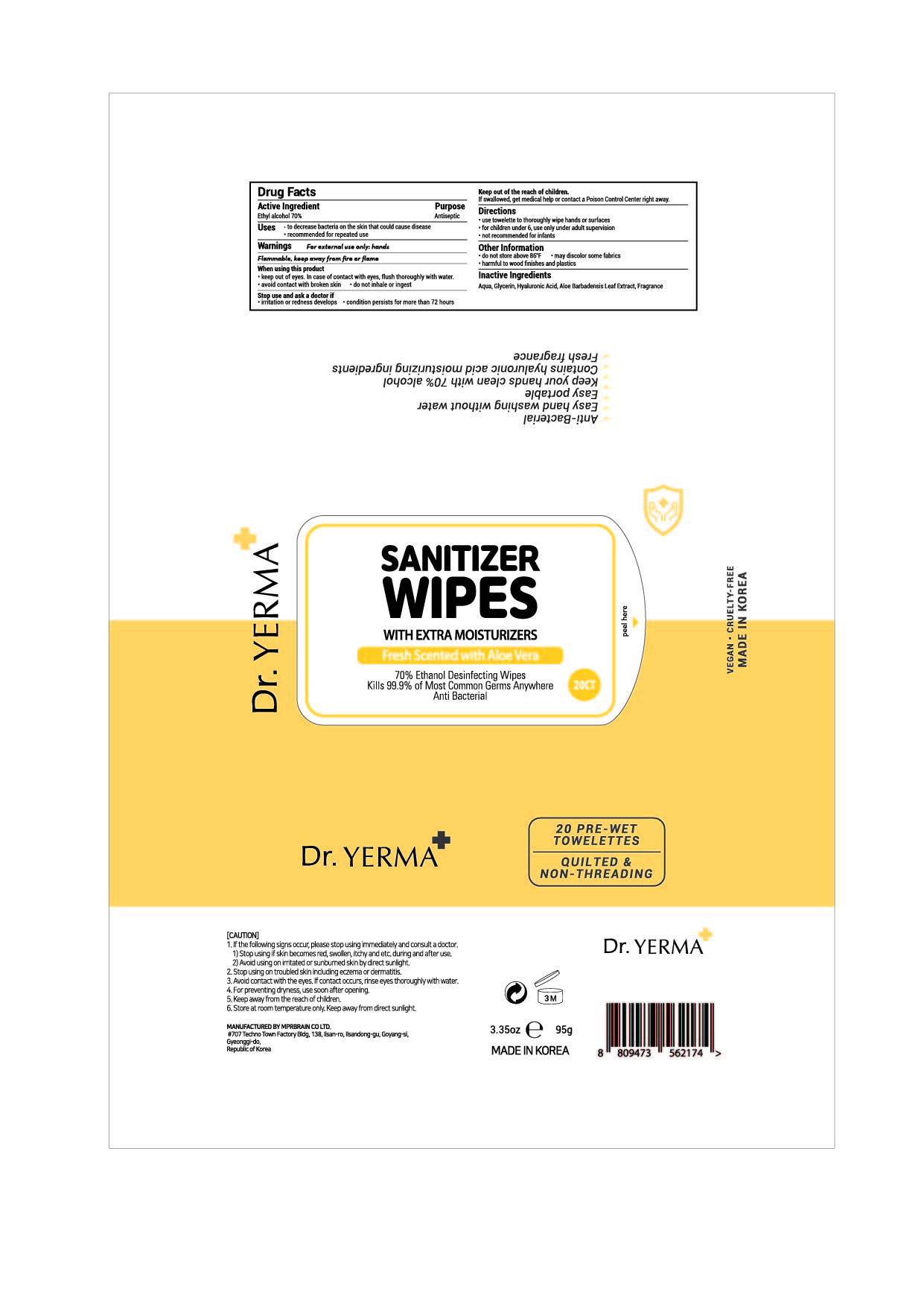 DRUG LABEL: Dr. YERMA SANITIZER WIPES Fresh Scented with Aloe Vera
NDC: 74741-0021 | Form: CLOTH
Manufacturer: MPRBRAIN CO.LTD
Category: otc | Type: HUMAN OTC DRUG LABEL
Date: 20210325

ACTIVE INGREDIENTS: ALCOHOL 3.325 g/1 1
INACTIVE INGREDIENTS: ALOE VERA LEAF; GLYCERIN; WATER; HYALURONIC ACID

[YELLOW PACKET] 74741-0021-1
Dr. YERMA SANITIZER WIPES Fresh Scented with Aloe Vera

PACKAGE LABEL

Active ingredient

Ethyl alcohol 70 %

Purpose

Antiseptic

Other Information

do not store above 86 °F

may discolor some fabrics

harmful to wood finishes and plastics

Inactive ingredients

Aqua, Glycerin, Hyaluronic Acid, Aloe Barbadensis Leaf Extract, Fragrance

Keep out of reach of children.

If swallowed, get medical help or contact a Poison Control Center right away.

When using this product

keep out of eyes. In case of contact with eyes, flush thoroughly with water.

avoid contact with broken skin.

do not inhale or ingest.

Directions

use towelette to thoroughly wipe hands or surfaces

for children under 6, use only under adult supervision

not recommended for infants

Warnings

For external use only: hands

Flammable, keep away from fire or flame.

Stop use and ask a doctor if

irritation or redness develops

conditions persists for more than 72 hours